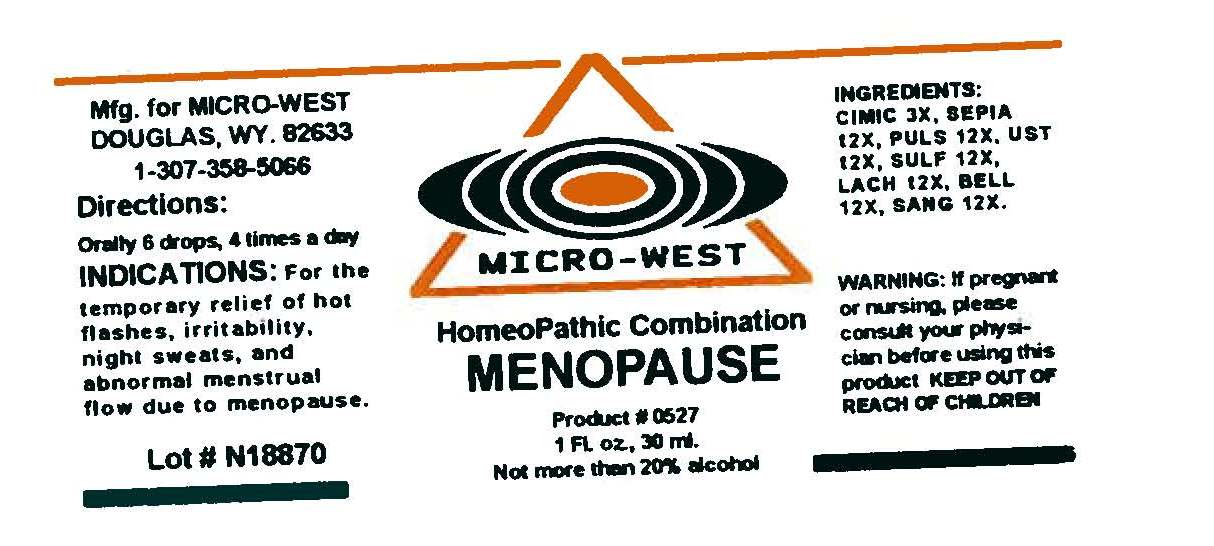 DRUG LABEL: MENOPAUSE
NDC: 61657-0527 | Form: LIQUID
Manufacturer: White Manufacturing Inc. DBA Micro-West
Category: homeopathic | Type: HUMAN OTC DRUG LABEL
Date: 19931201

ACTIVE INGREDIENTS: BLACK COHOSH 3 [hp_X]/30 mL; SEPIA OFFICINALIS JUICE 12 [hp_X]/30 mL; PULSATILLA VULGARIS 12 [hp_X]/30 mL; USTILAGO MAYDIS 12 [hp_X]/30 mL; SULFUR 12 [hp_X]/30 mL; LACHESIS MUTA VENOM 12 mL/30 mL; ATROPA BELLADONNA 12 [hp_X]/30 mL; SANGUINARIA CANADENSIS ROOT 12 [hp_X]/30 mL
INACTIVE INGREDIENTS: ALCOHOL

DRUG FACTS

ACTIVE INGREDIENTS

CIMICIFUGA RACEMOSA [HPUS] 3X

SEPIA [HPUS] 12X

PULSATILLA [HPUS] 12X

USTILAGO MAIDIS [HPUS] 12X

SULFUR 12X
LACHESIS MUTUS [HPUS) 12X
BELLADONNA [HPUS 12X
SANGUINARIA 12X

PURPOSE

FOR THE TEMPORARY RELIEF OF HOT FLASHES, IRRITABILITY, NIGHT SWEATS, AND ABNORMAL MENSTRUAL FLOW DUE TO MENOPAUSE

KEEP OUT OF REACH OF CHILDREN

INDICATIONS

INDICATIONS: FOR THE TEMPORARY RELIEF OF HOT FLASHES, IRRITABILITY, NIGHT SWEATS, AND ABNORMAL MENSTRUAL FLOW DUE TO MENOPAUSE

WARNING

WARNING: IF PREGNANT OR NURSING, PLEASE CONSULT YOUR PHYSICIAN BEFORE USING THIS PRODUCT

DIRECTIONS

DIRECTIONS: ORALLY 6 DROPS, 4 TIMES A DAY

INACTIVE INGREDIENTS

NOT MORE THAN 20% ALCOHOL

MANUFACTURE

MANUFACTURED FOR MICRO-WEST

DOUGLAS, WY 82633

1-307-358-5066